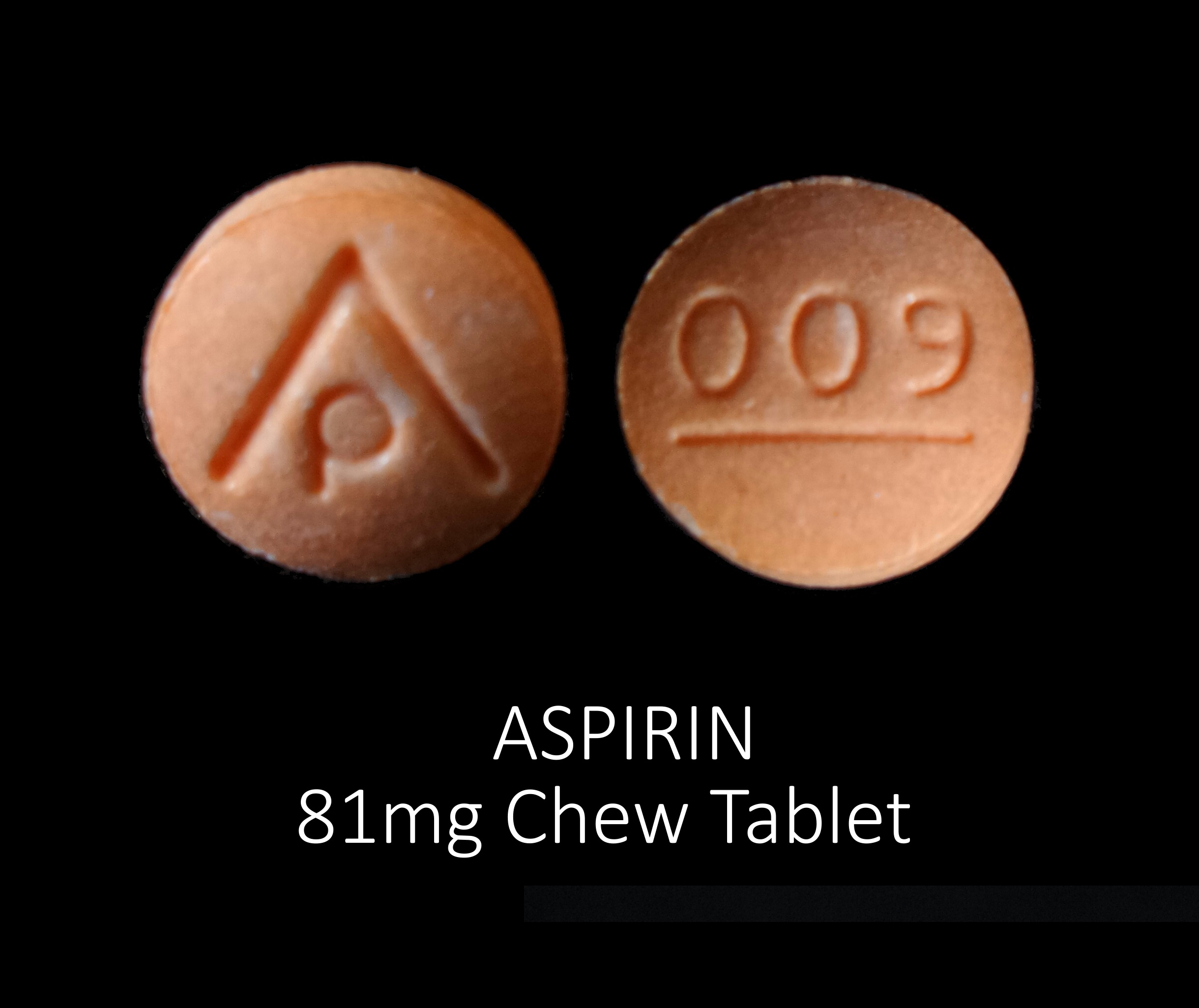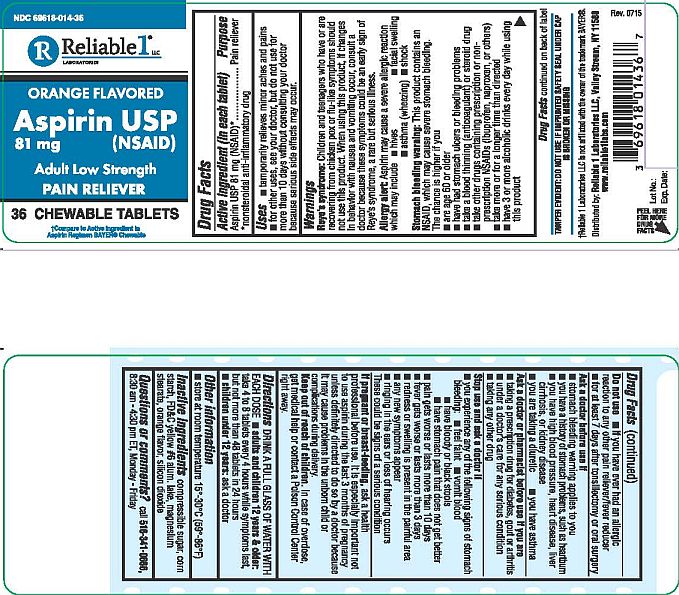 DRUG LABEL: Aspirin 81 mg
NDC: 69618-014 | Form: TABLET, CHEWABLE
Manufacturer: Reliable 1 Laboratories LLC
Category: otc | Type: HUMAN OTC DRUG LABEL
Date: 20230329

ACTIVE INGREDIENTS: ASPIRIN 81 mg/1 1
INACTIVE INGREDIENTS: STARCH, CORN; SILICON DIOXIDE; SUCROSE; FD&C YELLOW NO. 6; MAGNESIUM STEARATE

Aspirin USP 81 mg Chewable Tablets

Drugs Facts

Active ingredients (in each tablet)

Aspirin USP 81 mg (NSAID)*

*nonsterodial anti-inflammatory drug

Purpose

Pain reliever

Uses

- temporarily relieaves minor aches and pains
- for other uses, see your doctor, but do not use for more than 10 days without consulting your doctor because serious side effects may occur

Warnings

Reye's syndrome: Children and teenagers who have or are recovering from chicken pox or flu-like symptoms should not use this product. When using this product, if changes in behavior with nausea and vomiting occur, consult a doctor because these symptoms chould be an early sign of Reye's syndrome, a rare but serious illness.

Allergy alert: Aspirin may cause a severe allergic reastion which may include:

- hives
- facial swelling
- asthma (wheezing)
- shock

Stomach bleeding warning: This product contains an NSID, which may cause severe stomach bleeding. The chance is higher if you

- are age 60 or older
- have had stomach ulcers or bleeding problems
- take a blood thinning (anticoagulant) or steriod drug
- take other drugs containing prescription or non-prescription NSAIDs (ibuprofen, naproxen, or others)
- take more or for a longer time than directed
- have 3 or more alcoholic drinks every day while using this product

Drug Facts continued on back of label

Do not use

- if you have ever had an allergic reaction to any other pain reliever/fever reducer
- for at least 7 days after tonsillectomy or oral surgery

Ask a doctor before use if

- stomach bleeding warning applies to you
- you have a history of stomach problems, such as heartburn
- you have high blood pressure, heart disease, liver cirrhosis, or kidney disease
- you are taking a diuretic
- you have asthma

Ask a doctor or pharmacist before use if you are

- taking a prescription drug for diabetes, gout or arthritis
- under a doctor's care for any serious condition
- taking any other drug

Stop use and ask a doctor if

- you experience any of the following signs of stomach bleeding:
  - feel faint
  - vomit blood
  - have bloody or black stools
  - have stomach pain that does not get better
- pain gets worse or lasts more than 10 days
- fever gets worse or lasts more than 3 days
- redness or swelling is present in the painful area
- any new symptoms appear
- ringing in the ears or loss of hearing occurs

These could be sings of a serious condition

Keep out of reach of children. Incase of overdose, get medical help or contact a Poison Control Center right away.

Directions

DRINK A FULL GLASS OF WATER WITH EACH DOSE

- adults and children 12 years & older: take 4 to 8 tablets every 4 hours while symptoms last, but not more than 48 tablets in 24 hours
- children under 12 years: ask a doctor

Other infomation

- Store at room temperature 15º-30ºC (59º-86ºF)

Inactive ingredients

compressible sugar, corn starch, FD&C yellow #6 alum. lake, magnesium stearate, orange flavor, silicon dioxide

Questions or comments?

call 516-341-0666, 8:30 am - 4:30 pm ET, Monday - Friday

TAMPER EVIDENT: DO NOT USE IF IMPRINTED SAFETY SEAL UNDER CAP IS BROKEN OR MISSING

*Reliable 1 Laboratories LLC is not affiliated with the owner of the trademark BAYER®.

Distributed by: Reliable 1 Laboratories LLC, Valley Stream, NY 11580

www.reliable1labs.com

PACKAGE LABEL

NDC 69618-014-36

ORANGE FLAVORED

Aspirin USP 81 mg (NSAID)

Adult Low Strength

PAIN RELIEVER

36 CHEWABLE TABLETS

*Compare to Active Ingredient in Aspirin Regimen BAYER® Chewable